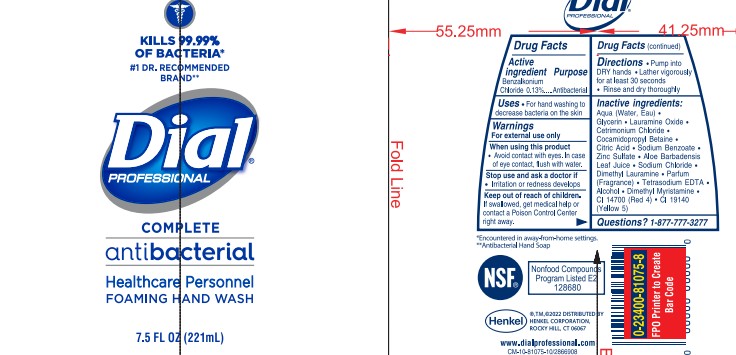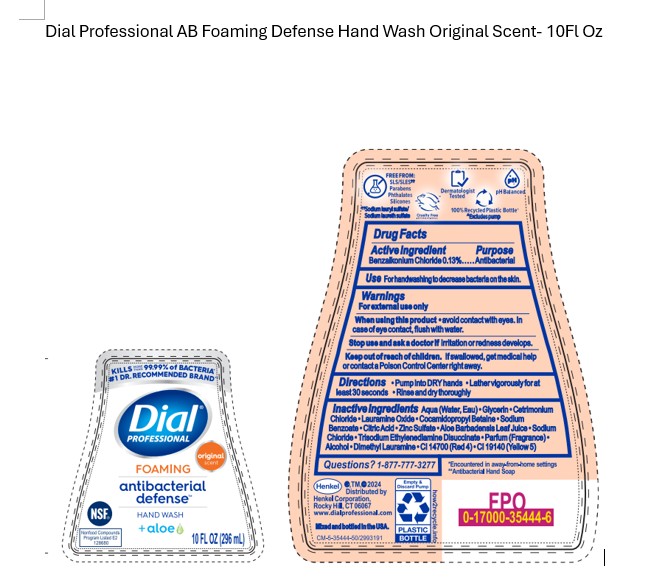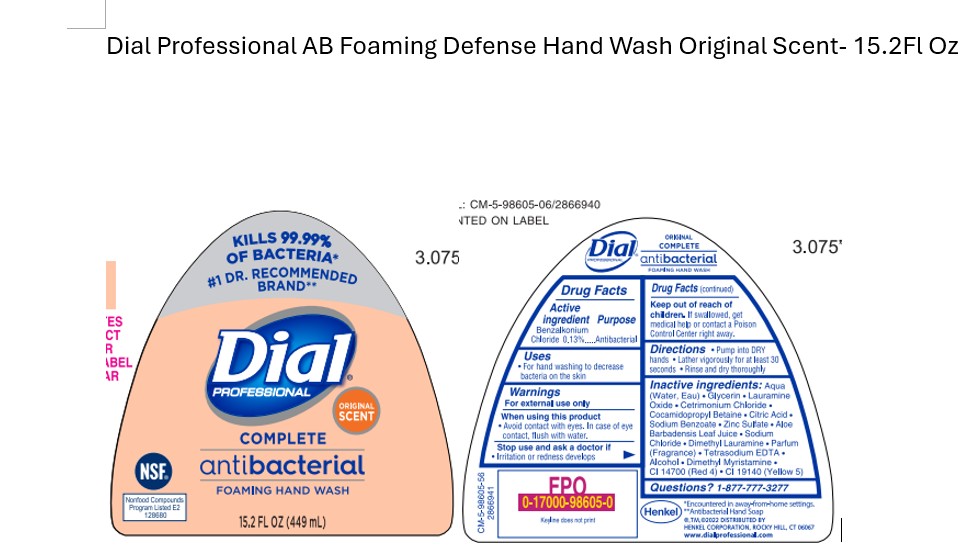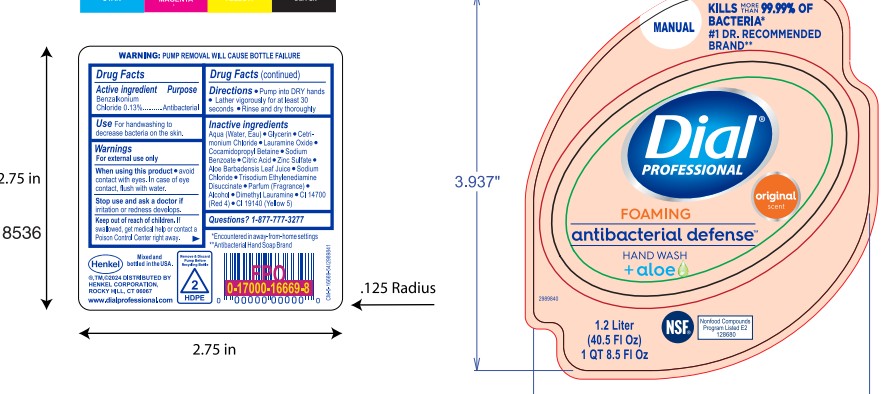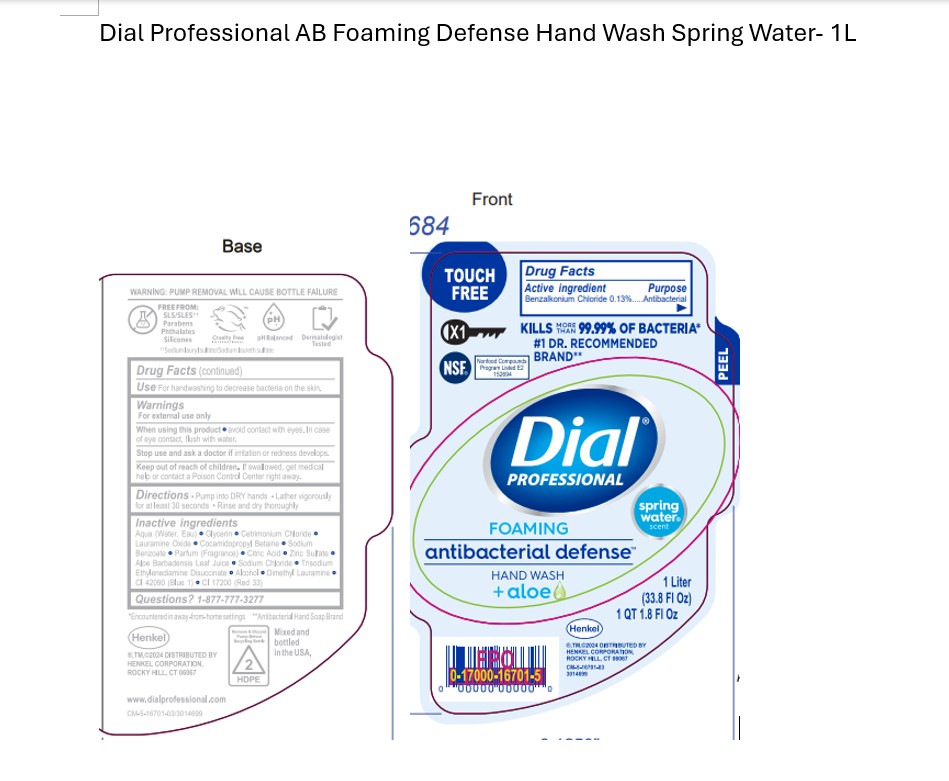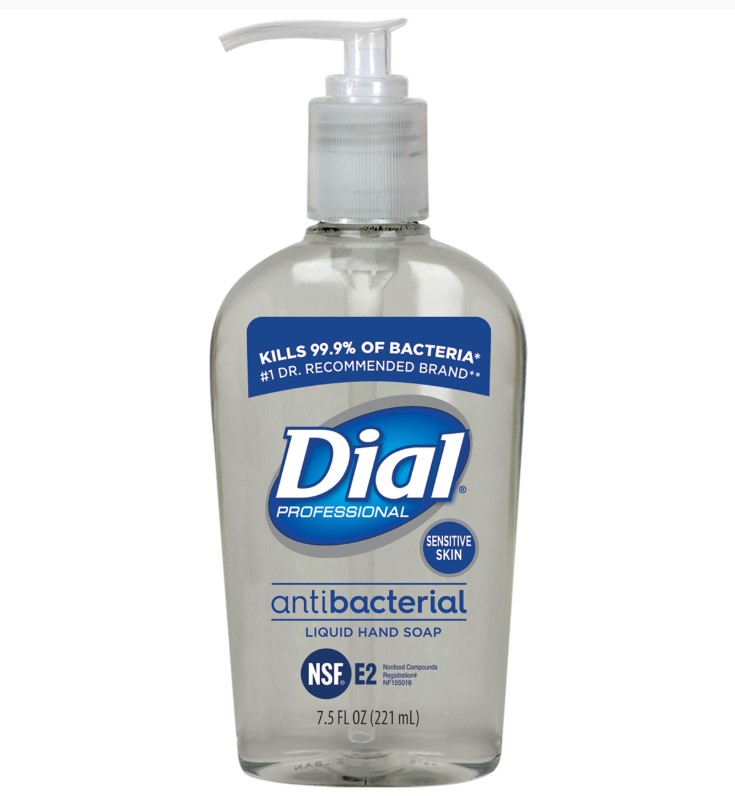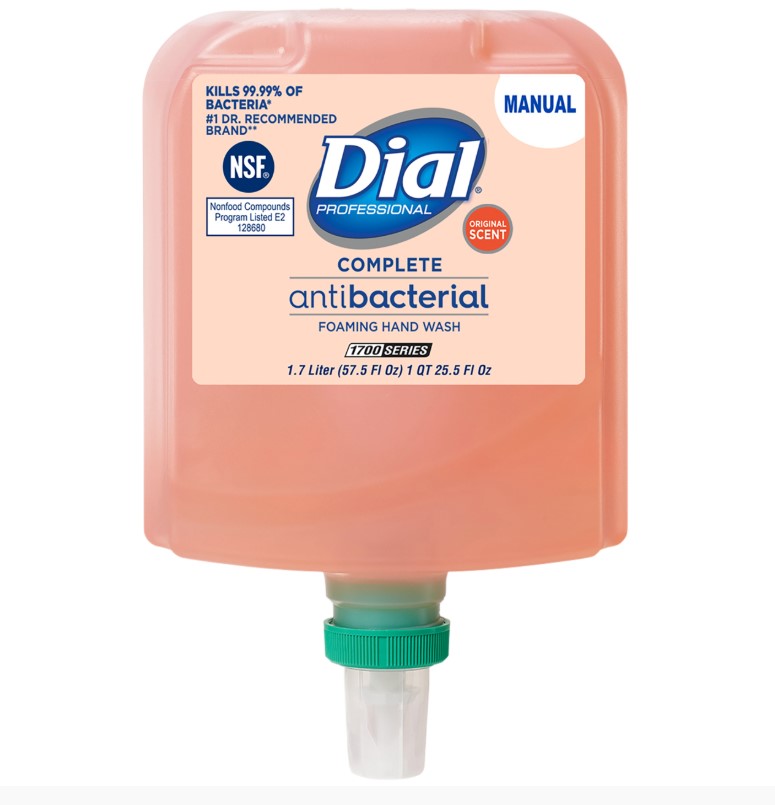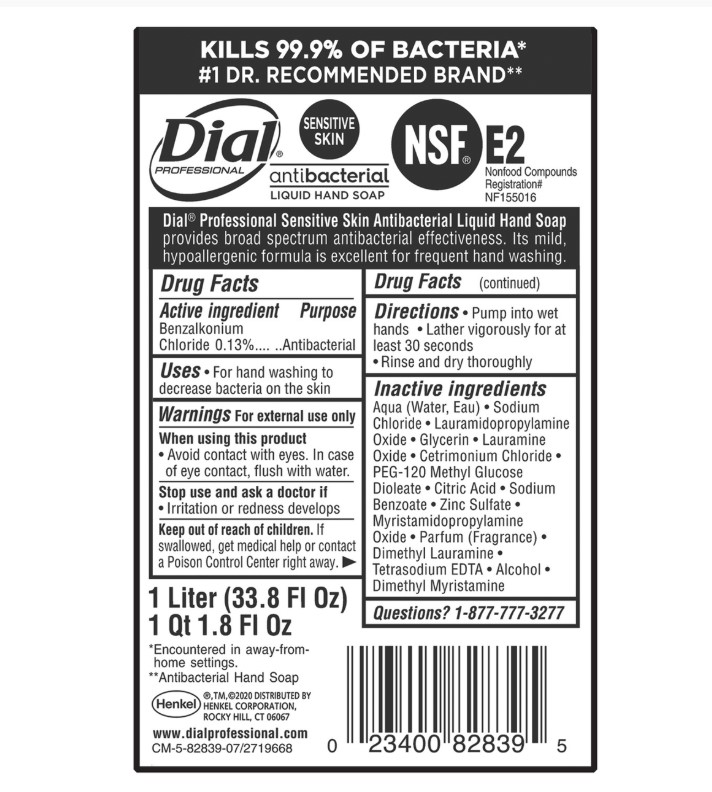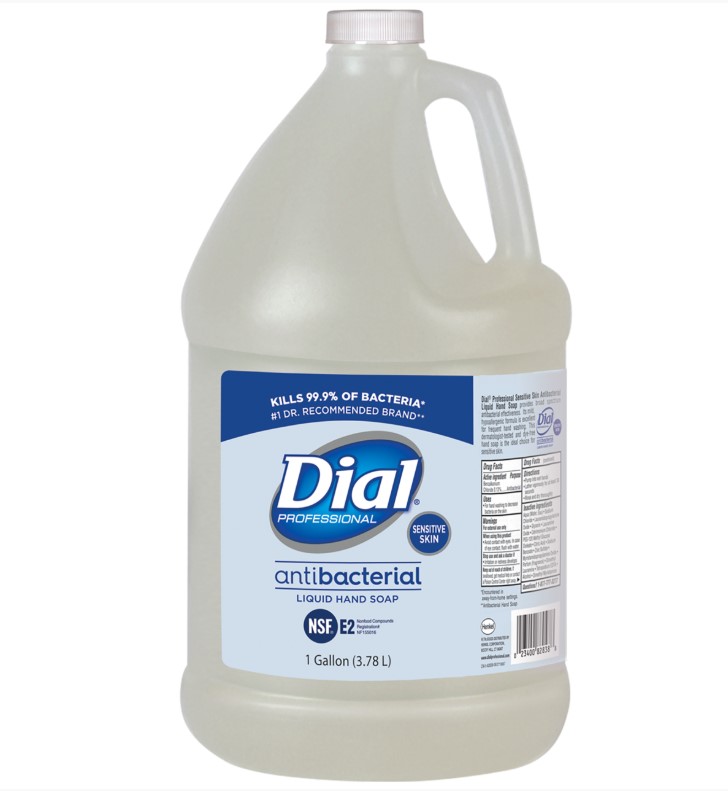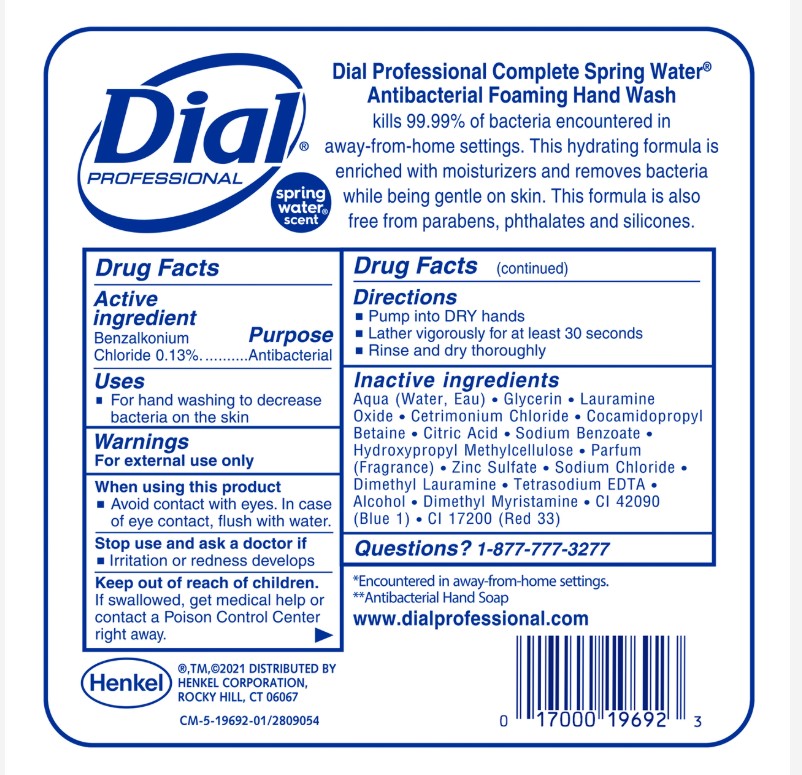 DRUG LABEL: Dial Professional Original Antibacterial Defense Foaming Hand wash plus Aloe
NDC: 54340-263 | Form: LIQUID
Manufacturer: Henkel Corporation
Category: otc | Type: HUMAN OTC DRUG LABEL
Date: 20251209

ACTIVE INGREDIENTS: BENZALKONIUM CHLORIDE 0.13 g/100 mL
INACTIVE INGREDIENTS: WATER 95.7 mL/100 mL

Dial® Professional Dial Complete Original Antibacterial Dial 1700 Universal Manual Refill - 3/1.7L
Dial® Professional Dial Complete Original Antimicrobial FHW Manual Total Clean
Dial® Professional Sensitive Skin Antibacterial Liquid Hand Soap - Refill 8/1L
Dial® Professional Sensitive Skin Antibacterial Liquid Hand Soap - Refill 4/1Gallon
Dial® Professional Sensitive Skin Antibacterial Defense Liquid Hand Soap Pump Bottle - 12/11oz
Dial® Professional Spring Water Antibacterial Liquid Hand Soap - Refill 4/1GallonDial Complete Spring Water Dial® Professional Antibacterial Dial 1700 Manual Refill - 3/1.7L
Dial® Professional Dial Complete Spring Water FIT X1 Manual - Refill 3/1.2L
Dial® Professional Dial Complete Spring Water FIT X2 Manual - Refill 3/1.2L
Dial® Professional Dial Complete Spring Water FIT X2 Touch Free - Refill 3/1L
Dial® Professional Clean + Gentle FIT Universal Manual Refill 3/1.2 L
Dial® Professional Clean + Gentle FIT Universal Touch-Free Refill 3/1 L
Dial® Professional Clean + Gentle Dial 1700 Refill 3/1.7 L
Dial® Professional Clean + Gentle FIT X1 Manual Refill 3/1.2 L
Dial® Professional Clean + Gentle FIT X1 Touch-Free Refill 3/1 L
Dial® Professional Clean + Gentle FIT X2 Manual Refill 3/1.2 L
Dial® Professional Clean + Gentle FIT X2 Touch-Free Refill 3/1 L
Dial® Professional Complete Antibacterial Foaming Hand Wash Original Scent Manual
Dial® Professional Complete Antibacterial Foaming Hand Wash Original Scent
Dial® Professional Complete Antibacterial Foaming Hand Wash Original Scent
Dial® Professional Antimicrobial Liquid Hand Soap
Dial® Professional Complete Antibacterial Foaming Hand Wash Original Scent
Dial® Professional Complete Antibacterial Foaming Hand Wash Original Scent Manual
Dial® Professional Complete Antibacterial Foaming Hand Wash Original Scent Manual X1
Dial® Professional Complete Antibacterial Foaming Hand Wash Original Scent TF X1
Dial® Professional Complete Antibacterial Foaming Hand Wash Original Scent Manual X2
Dial® Professional Complete Antibacterial Foaming Hand Wash Original Scent TF X2
Dial Professional Original Antibacterial Defense Foaming Hand Wash Plus Aloe
Dial Professional Foaming Antibacterial defense hand wash Plus Aloe Spring Water
Dial Professional Basics Hypoallergenic Foaming Hand Wash1 Gallon Refill

Dial® Professional Complete Original Antibacterial Dial 1700 Universal Manual Refill Dial® Professional Sensitive Skin Antibacterial Liquid Hand Soap Dial Prof Antibacterial Liquid Hand Soap Spring Water Refill

Dial Professional Sensitive Skin Antibacterial Liquid Hand Soap

Aqua (Water, Eau)
Lauramidopropylamine Oxide
Glycerin
Cetrimonium Chloride
Sodium Chloride
Lauramine Oxide
PEG-120 Methyl Glucose Dioleate
Citric Acid
Sodium Benzoate
Myristamidopropylamine Oxide
Benzalkonium Chloride
Zinc Sulfate
Aloe Barbadensis Leaf Juice
Trisodium Ethylenediamine Disuccinate
Dimethyl Lauramine
Alcohol
Dimethyl Myristamine

Dial Professional Antibacterial Foaming Hand Soap Spring Water Scent

Aqua
Glycerin
Cetrimonium Chloride
Lauramine Oxide
Cocamidopropyl Betaine
Sodium Benzoate
Parfum
Benzalkonium Chloride
Citric Acid
Zinc Sulfate
Aloe Barbadensis Leaf Juice
Sodium Chloride
Trisodium Ethylenediamine Disuccinate
Alcohol
Dimethyl Lauramine
Dimethyl Myristamine
CI 42090
CI 17200

Dial Professional Antibacterial Hand Soap Spring Water Scent

Aqua
Sodium Chloride
Lauramidopropylamine Oxide
Glycerin
Cetrimonium Chloride
Lauramine Oxide
PEG-120 Methyl Glucose Dioleate
Citric Acid
Sodium Benzoate
Parfum
Myristamidopropylamine Oxide
Benzalkonium Chloride
Aloe Barbadensis Leaf Juice
Zinc Sulfate
Trisodium Ethylenediamine Disuccinate
Dimethyl Lauramine
Alcohol
CI 42090
CI 17200
Hexyl Cinnamal

Dial Professional Clean and Gentle Antibacterial Foaming Hand Soap

Aqua (Water, Eau)

Glycerin
Lauramine Oxide
Cetrimonium Chloride
Cocamidopropyl Betaine
Citric Acid
Sodium Benzoate
Benzalkonium Chloride
Zinc Sulfate
Sodium Chloride
Dimethyl Lauramine
Tetrasodium EDTA
Alcohol
Dimethyl Myristamine

Dial Professional Complete Antibacterial Foaming Hand Wash Original Scent

Aqua (Water, Eau)

Glycerin
Cetrimonium Chloride
Lauramine Oxide
Cocamidopropyl Betaine
Sodium Benzoate
Benzalkonium Chloride
Citric Acid
Zinc Sulfate
Aloe Barbadensis Leaf Juice
Sodium Chloride
Trisodium Ethylenediamine Disuccinate
Parfum (Fragrance)
Alcohol
Dimethyl Lauramine
CI 14700 (Red 4)
CI 19140 (Yellow 5)

Warnings

Warnings For external use only

When using this product•Avoid contact with eyes •

Stop use and ask a doctor if•Irritation or redness develops OR Stop use and ask a doctor ifirritation or redness develops
Keep out of reach of children. •If swallowed, get medical help or contact a Poison Control Center right away

DOSAGE AND ADMINISTRATION

Directions . Pump into wet
hands . Lather vigorously for at
least 30 seconds
. Rinse and dry thoroughly

Uses

For hand washing to decrease bacteria on the skin

Dial Professional Original Gold Antibacterial Liquid Hand Soap

Benzalkonium Chloride

Purpose

Purpose: Antibacterial